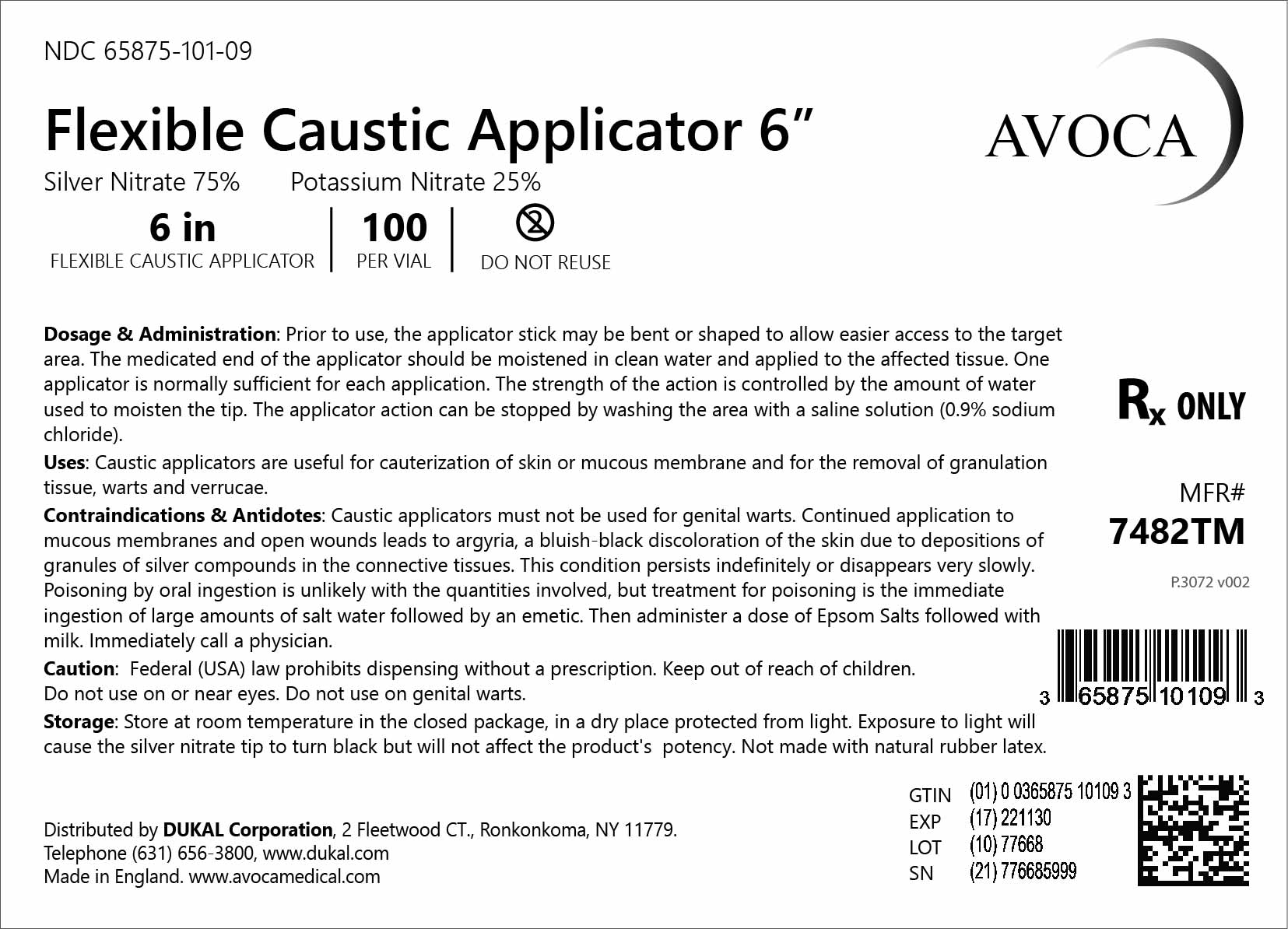 DRUG LABEL: Avoca Flexible Caustic Applicator
NDC: 65875-101 | Form: STICK
Manufacturer: Bray Group Limited
Category: prescription | Type: HUMAN PRESCRIPTION DRUG LABEL
Date: 20210119

ACTIVE INGREDIENTS: SILVER NITRATE 30 mg/40 mg
INACTIVE INGREDIENTS: POTASSIUM NITRATE 10 mg/40 mg

Dosage & Administration

Prior to use, the applicator stick may be bent or shaped to allow easier access to the target area. The medicated end of the applicator should be moistened in clean water and applied to the affected tissue. One applicator is normally sufficient for each application. The strength of the action is controlled by the amount of water used to moisten the tip. The applicator action can be stopped by washing the area with a saline solution (0.9% sodium chloride).

Uses

Caustic applicators are useful for cauterization of skin or mucous membrane and for the removal of granulation tissue, warts and verrucae.

Contraindications & Antidotes

Caustic applicators must not be used for genital warts. Continued application to mucous membranes and open wounds leads to argyria, a bluish-black discoloration of the skin due to depositions of granules of silver compounds in the connective tissues. This condition persists indefinitely or disappears very slowly. Poisoning by oral ingestion is unlikely with the quantities involved, but treatment for poisoning is the immediate ingestion of large amounts of salt water followed by an emetic. Then administer a dose of Epsom Salts followed with milk. Immediately call a physician.

Caution

KEEP OUT OF REACH OF CHILDREN. DO NOT USE ON OR NEAR EYES.

Storage

Store at room temperature in the closed package, in a dry place protected from light. Exposure to light will cause the silver nitrate tip to turn black, but will not affect the product's potency. Not made with natural rubber latex.

PACKAGE LABEL

Image of label02: